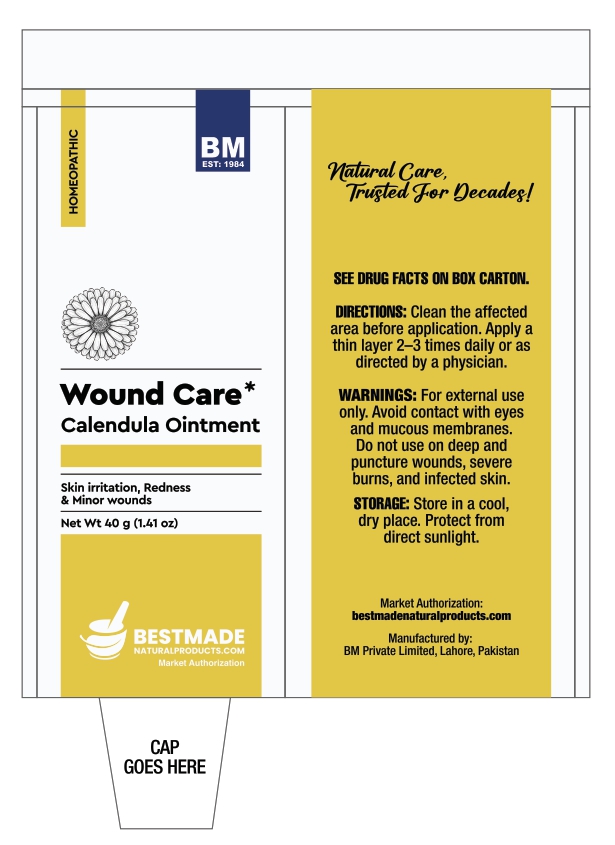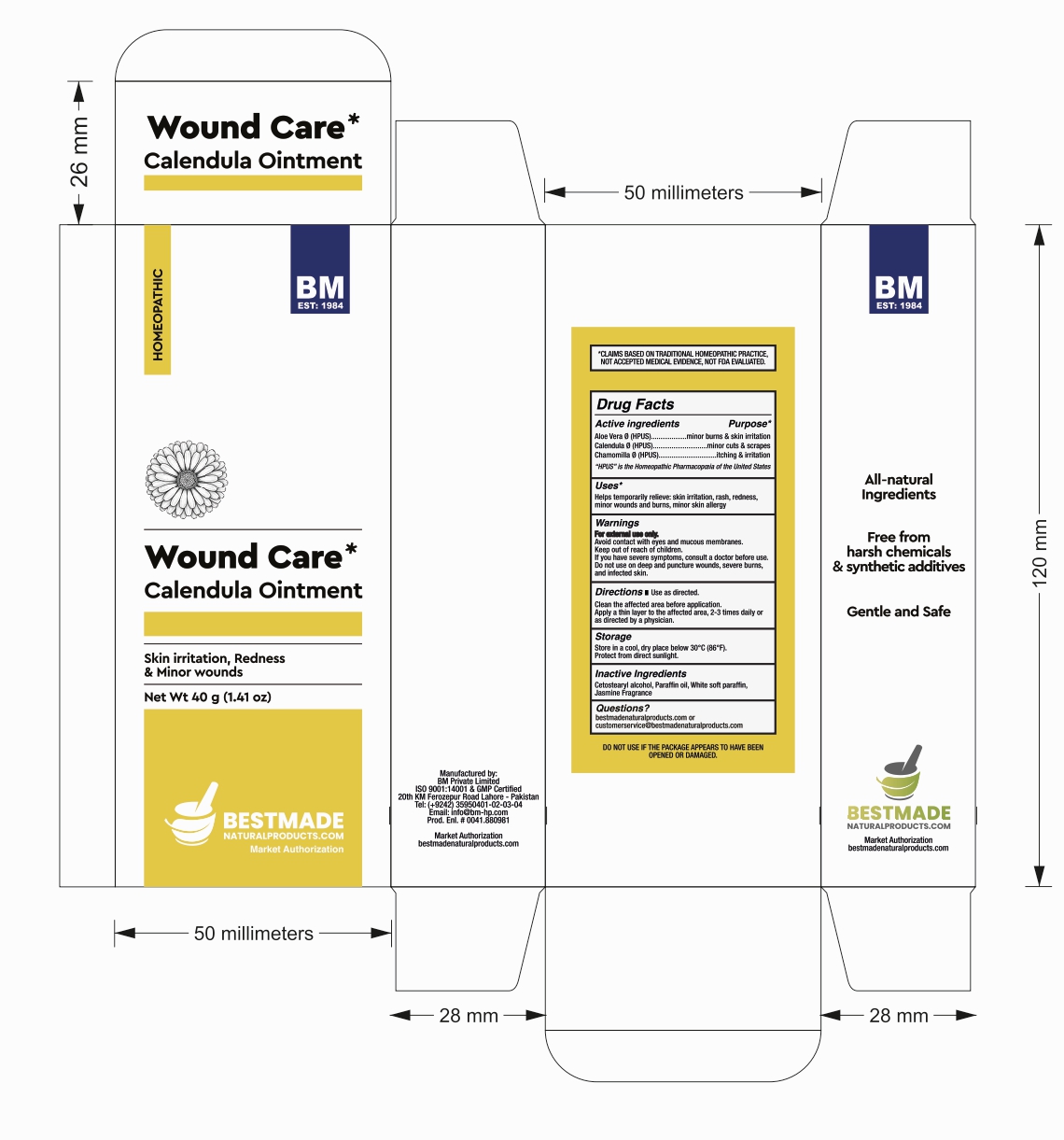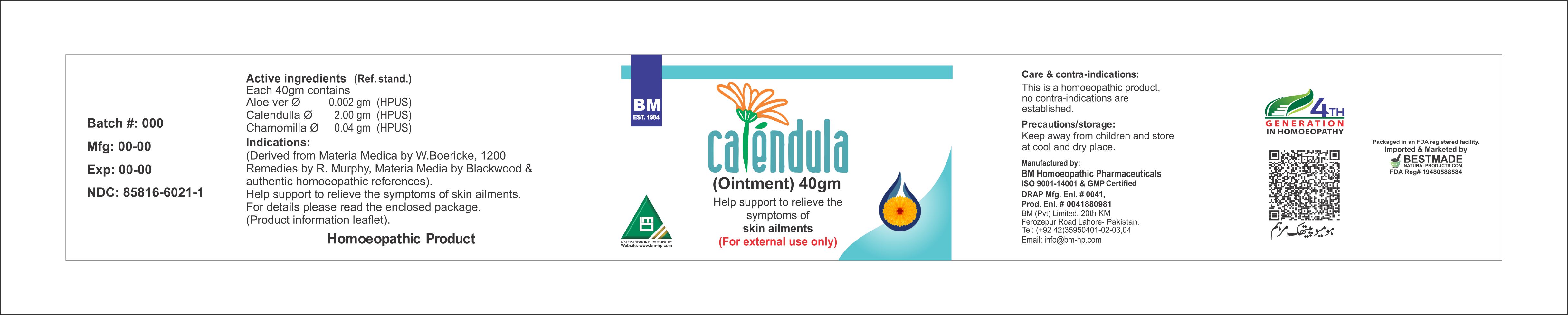 DRUG LABEL: BM Calendula
NDC: 85816-6021 | Form: OINTMENT
Manufacturer: BM Private Limited
Category: homeopathic | Type: HUMAN OTC DRUG LABEL
Date: 20260212

ACTIVE INGREDIENTS: ALOE VERA LEAF 1 [hp_X]/1 g; CALENDULA OFFICINALIS FLOWERING TOP 1 [hp_X]/1 g; CHAMOMILE 1 [hp_X]/1 g
INACTIVE INGREDIENTS: JASMINUM OFFICINALE FLOWER 0.0025 g/1 g; CETOSTEARYL ALCOHOL 0.095 g/1 g; MINERAL OIL 0.04 g/1 g; WHITE PETROLATUM 0.8625 g/1 g

BM Calendula Ointment

Inactive Ingredients:

Cetostearyl alcohol, Paraffin oil, White soft paraffin, Jasmine Fragrance

Active ingredients

Aloe Vera Ø (HPUS)

Calendula Ø (HPUS)

Chamomilla Ø (HPUS)

Uses*

Helps temporarily relieve: skin irritation, rash, redness, minor wounds and burns, minor skin allergy

Active ingredients Purpose*

Aloe Vera Ø (HPUS)……………. minor burns & skin irritation

Calendula Ø (HPUS)……………minor cuts & scrapes

Chamomilla Ø (HPUS)…………….itching & irritation

Directions:

Use as directed.

Clean the affected area before application.

Apply a thin layer to the affected area, 2-3 times daily or as directed by a physician.

Warnings:

For external use only.

Avoid contact with eyes and mucous membranes.

Keep out of reach of children.

If you have severe symptoms, consult a doctor before use.

Do not use on deep and puncture wounds, severe burns, and infected skin.

Warnings:

Keep out of reach of children.

Storage:

Store in a cool, dry place below 30°C (86°F).

Protect from direct sunlight.

Package 1: jar label

Package 2: Tube

Carton Box